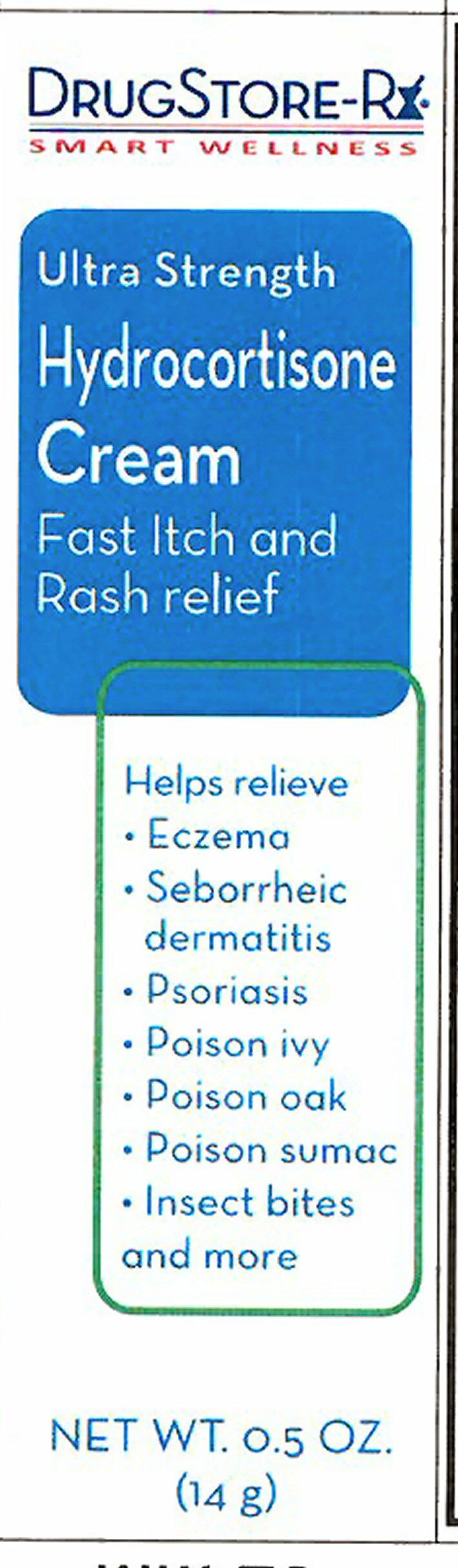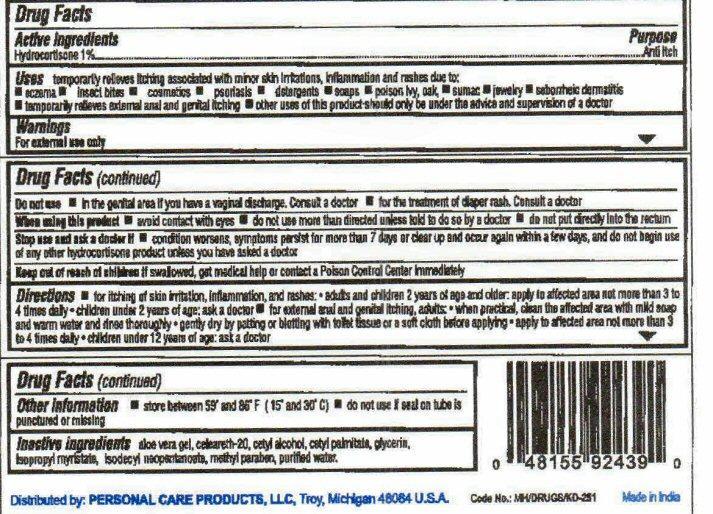 DRUG LABEL: Hydrocortisone
NDC: 29500-2439 | Form: CREAM
Manufacturer: Personal Care Products, Inc.
Category: otc | Type: HUMAN OTC DRUG LABEL
Date: 20130710

ACTIVE INGREDIENTS: HYDROCORTISONE 140 mg/14 g
INACTIVE INGREDIENTS: ALOE VERA LEAF; POLYOXYL 20 CETOSTEARYL ETHER; CETYL ALCOHOL; CETYL PALMITATE; GLYCERIN; ISOPROPYL MYRISTATE; ISODECYL NEOPENTANOATE; METHYLPARABEN; WATER

Active Ingredient

Drug Facts

Hydrocortisone 1%

Purpose

Anti itch

Keep out of reach of children. If swallowed, get medical help or contact a Poison Control Center right away.

Uses

temporarily relieves itching associated with minor skin irritations, inflammation and rashes due to:

- eczema
- inset bites
- cosmetics
- psoriasis
- detergents
- soaps
- poison ivy, oak
- sumac
- jewelry
- seborrheic dermatitis
- temporarily relieves external anal and genital itching
- other uses of this product should only be under the advice and supervision of a doctor

Warnings

For external use only
Do not use

- in the genital area if you have a vaginal discharge. Consult a doctor.
- for the treatment of diaper rash. Consult a doctor

When using this product

- avoid contact with eyes
- do not use more than directed unless told to do so by a doctor
- do not put directly into the rectum

Stop use and ask a doctor if

- condition worsens, symptoms persist for more than 7 days or clear up and occur again within a few days, and do not begin use of any other hydrocortisone product unless you have asked a doctor

Directions

- for itching of skin irritation, inflammation, and rashes: adults and children 2 years of age and older: apply to affected area not more than 3 to 4 times daily - children under 2 years of age: ask a doctor

- for external anal and genital itching: adults - when practical, clean the affected area with mild soap and warm water and rinse thoroughly - gently dry by patting or blotting with toilet tissue or a soft cloth before applying - apply to affected area not more than 3 to 4 times daily - children under 12 years of age: ask a doctor

Other information

- store between 59° and 86° F (15° and 30° C)
- do not use if seal on tube is punctured or missing

Inactive ingredients

aloe vera gel, celeareth-20, cetyl alcohol, cetyl palitate, glycerin, isopropyl myristate, isodecyl neopentanoate, methyl paraben, purified water

Product Label

DRUGSTORE-Rx
SMART WELLNESS
Ultra Strength
Hydrocortisone Cream
Fast Itch and Rash relief
Helps relieve

- Eczema
- Seborrheic dermatitis
- Psoriasis
- Poison ivy
- Poison oak
- Poison sumac
- Insect bites and more

NET WT. 0.5 OZ. (14 g)
Distributed by: PERSONAL CARE PRODUCTS, LLC Troy, Michigan 48084 U.S.A.
Code No.:MH/DRUGS/KD-313 Made in India